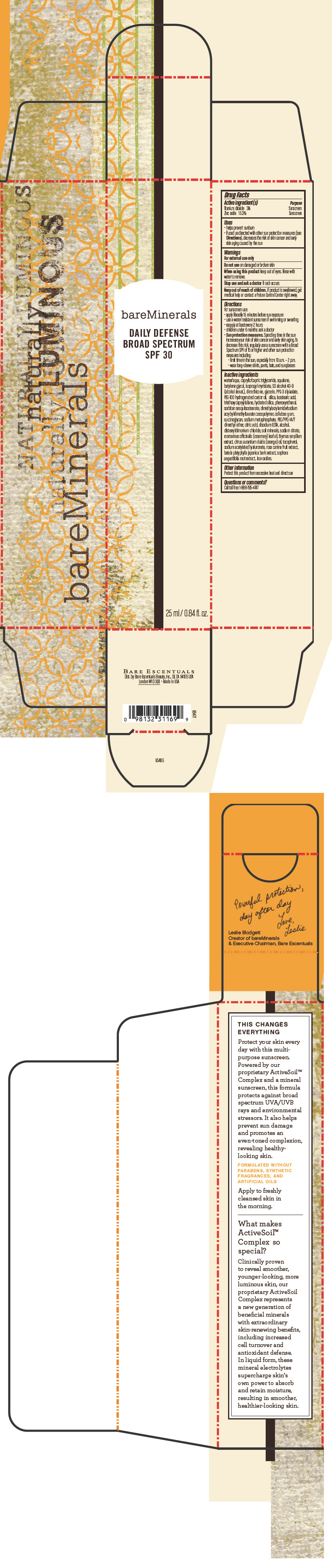 DRUG LABEL: bareMinerals Daily Defense Broad Spectrum SPF 30
NDC: 98132-724 | Form: LOTION
Manufacturer: Bare Escentuals Beauty, Inc.
Category: otc | Type: HUMAN OTC DRUG LABEL
Date: 20140212

ACTIVE INGREDIENTS: Titanium Dioxide 30 mg/1 mL; Zinc Oxide 1530 mg/1 mL
INACTIVE INGREDIENTS: WATER; MEDIUM-CHAIN TRIGLYCERIDES; SQUALANE; BUTYLENE GLYCOL; ISOPROPYL MYRISTATE; DIMETHICONE; GLYCERIN; SILICON DIOXIDE; ISOSTEARIC ACID; TRIETHOXYCAPRYLYLSILANE; HYDRATED SILICA; PHENOXYETHANOL; CARBOXYMETHYLCELLULOSE SODIUM; PEG/PPG-14/7 DIMETHYL ETHER; CITRIC ACID MONOHYDRATE; EDETATE DISODIUM; ALCOHOL; DISTEARYLDIMONIUM CHLORIDE; SODIUM CITRATE; ROSEMARY OIL; THYMUS SERPYLLUM; ORANGE OIL; TOCOPHEROL; SODIUM ACETYLATED HYALURONATE; ROSA CANINA FRUIT; BETULA PLATYPHYLLA BARK; SOPHORA FLAVESCENS ROOT; FERRIC OXIDE RED

bareMinerals Daily Defense Broad Spectrum SPF 30

Drug Facts

ACTIVE INGREDIENT

Active ingredient(s) | Purpose
Titanium dioxide 3% | Sunscreen
Zinc oxide 15.3% | Sunscreen

Uses

- helps prevent sunburn
- if used as directed with other sun protection measures (see Directions), decreases the risk of skin cancer and early skin aging caused by the sun

Warnings

For external use only

Do not use on damaged or broken skin

When using this product keep out of eyes. Rinse with water to remove.

Stop use and ask a doctor if rash occurs

Keep out of reach of children. If product is swallowed, get medical help or contact a Poison Control Center right away.

Directions

For sunscreen use:

- apply liberally 15 minutes before sun exposure
- use a water resistant sunscreen if swimming or sweating
- reapply at least every 2 hours
- children under 6 months: ask a doctor
- Sun protection measures. Spending time in the sun increases your risk of skin cancer and early skin aging. To decrease this risk, regularly use a sunscreen with a Broad Spectrum SPF of 15 or higher and other sun protection measures including:
  - limit time in the sun, especially from 10 a.m. – 2 p.m.
  - wear long-sleeve shirts, pants, hats, and sunglasses

Inactive ingredients

water/aqua, caprylic/capric triglyceride, squalane, butylene glycol, isopropyl myristate, SD alcohol 40-B (alcohol denat.), dimethicone, glycerin, PPG-3 dipivalate, PEG-100 hydrogenated castor oil, silica, isostearic acid, triethoxycaprylylsilane, hydrated silica, phenoxyethanol, sorbitan sesquiisostearate, dimethylacrylamide/sodium acryloyldimethyltaurate crosspolymer, cellulose gum, succinoglycan, sodium metaphosphate, PEG/PPG-14/7 dimethyl ether, citric acid, disodium EDTA, alcohol, distearyldimonium chloride, soil minerals, sodium citrate, rosmarinus officinalis (rosemary) leaf oil, thymus serpillum extract, citrus aurantium dulcis (orange) oil, tocopherol, sodium acetylated hyaluronate, rosa canina fruit extract, betula platyphylla japonica bark extract, sophora angustifolia root extract, iron oxides.

Other information

Protect this product from excessive heat and direct sun

Questions or comments?

Call toll free 1-888-795-4747

Dist. by Bare Escentuals Beauty, Inc., SF, CA 94105 USA

PRINCIPAL DISPLAY PANEL - 25 mL Tube Carton

bareMinerals

DAILY DEFENSE
BROAD SPECTRUM
SPF 30

25 ml / 0.84 fl. oz.